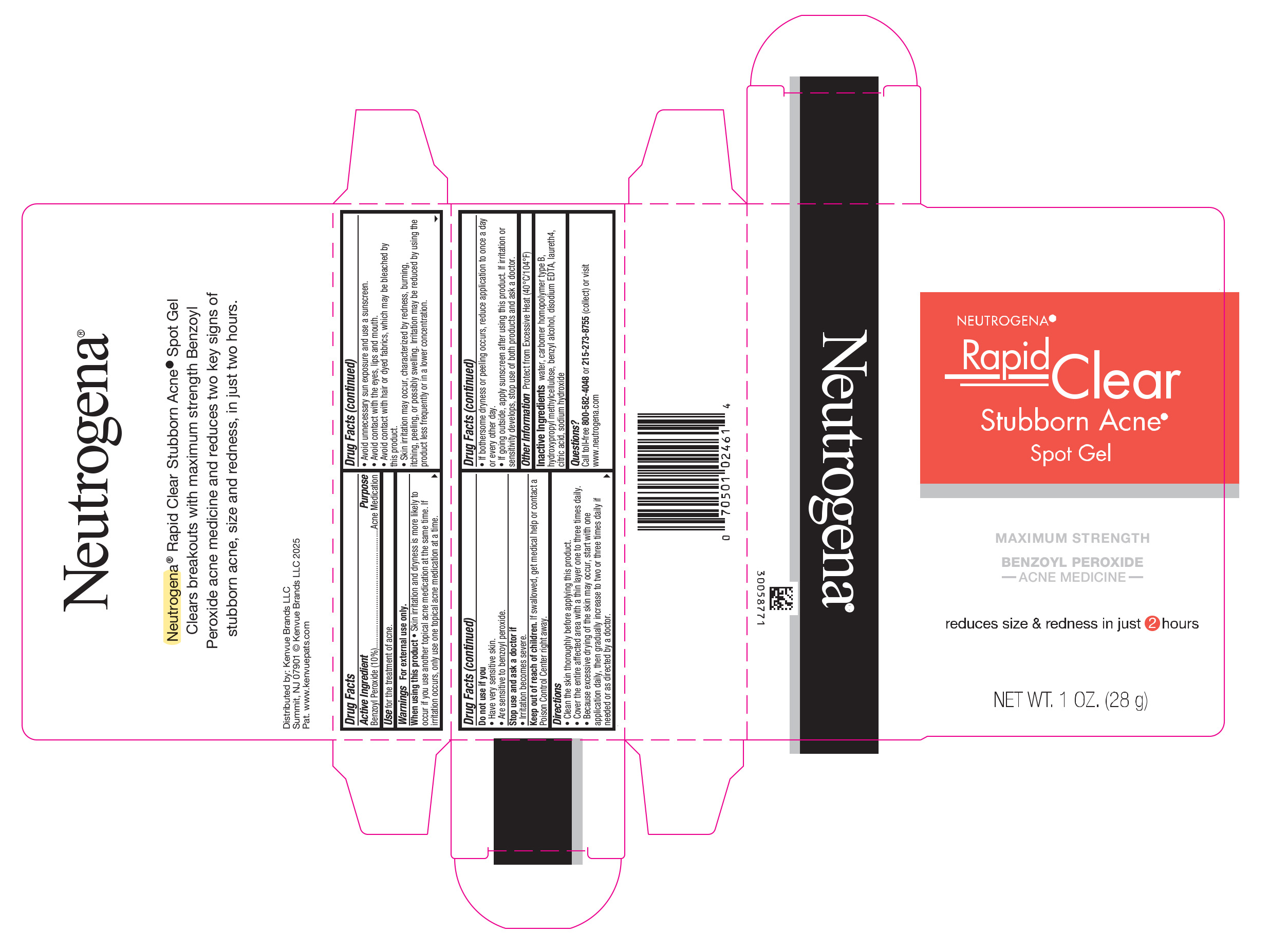 DRUG LABEL: Neutrogena Rapid Clear Stubborn Acne Spot
NDC: 69968-0043 | Form: GEL
Manufacturer: Kenvue Brands LLC
Category: otc | Type: HUMAN OTC DRUG LABEL
Date: 20250512

ACTIVE INGREDIENTS: BENZOYL PEROXIDE 100 mg/1 g
INACTIVE INGREDIENTS: CITRIC ACID MONOHYDRATE; SODIUM HYDROXIDE; WATER; CARBOMER HOMOPOLYMER TYPE B (ALLYL PENTAERYTHRITOL OR ALLYL SUCROSE CROSSLINKED); HYPROMELLOSE, UNSPECIFIED; BENZYL ALCOHOL; EDETATE DISODIUM; LAURETH-4

Neutrogena® Rapid Clear® Stubborn Acne Spot Gel

Drug Facts

Active Ingredients

Benzoyl Peroxide (10%)

Purpose

Acne Medication

Use

For the treatment of acne.

Warnings

For external use only.

When using this product

- Skin irritation and dryness is more likely to occur if you use another topical acne medication at the same time. If irritation occurs, only use one topical acne medication at a time.
- Avoid unnecessary sun exposure and use a sunscreen.
- Avoid contact with the eyes, lips and mouth.
- Avoid contact with hair or dyed fabrics, which may be bleached by this product.
- Skin irritation may occur, characterized by redness, burning, itching, peeling, or possibly swelling. Irritation may be reduced by using the product less frequently or in a lower concentration.

Do not use if

- Have very sensitive skin.
- Are sensitive to benzoyl peroxide.

Stop use and ask a doctor if

- Irritation becomes severe.

Keep out of reach of children. If swallowed, get medical help or contact a Poison Control Center right away.

Directions

- Clean the skin thoroughly before applying this product.
- Cover the entire affected area with a thin layer one to three times daily.
- Because excessive drying of the skin may occur, start with one application daily, then gradually increase to two or three times daily if needed or as directed by a doctor.
- If bothersome dryness or peeling occurs, reduce application to once a day or every other day.
- If going outside, apply sunscreen after using this product. If irritation or sensitivity develops, stop use of both products and ask a doctor.

Other Information

Protect from Excessive Heat (40 °C/104 °F)

Inactive Ingredients

water, carbomer homopolymer type B, hydroxypropyl methylcellulose, benzyl alcohol, disodium EDTA, laureth-4, citric acid, sodium hydroxide

Questions?

Call toll-free 800-582-4048 or 215-273-8755 (collect) or visit www.neutrogena.com

Distributed by: Kenvue Brands LLC .
Summit, NJ 07901

PRINCIPAL DISPLAY PANEL - 28 g Tube Carton

NEUTROGENA®

Rapid
Clear

Stubborn Acne®
Spot Gel

MAXIMUM STRENGTH
BENZOYL PEROXIDE
ACNE MEDICINE
reduces size & redness in just 2 hours

NET WT. 1 OZ. (28g)